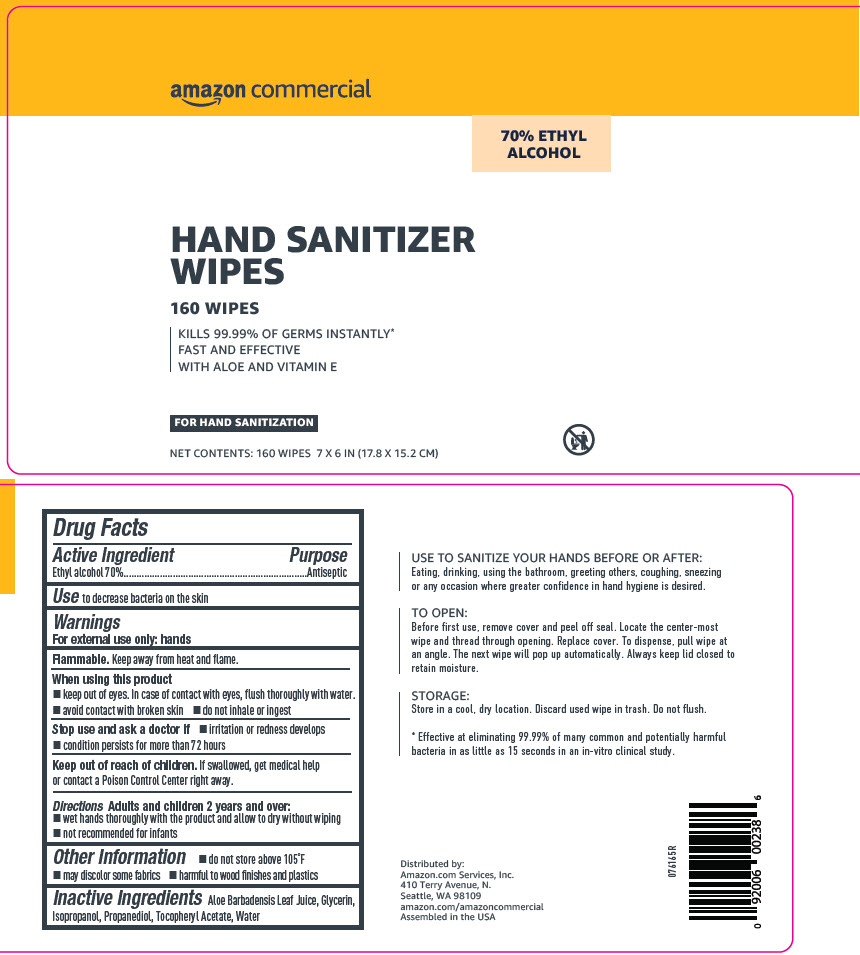 DRUG LABEL: Amazon Commercial Hand Sanitizer Wipes
NDC: 72288-999 | Form: CLOTH
Manufacturer: Amazon.com Services LLC
Category: otc | Type: HUMAN OTC DRUG LABEL
Date: 20200417

ACTIVE INGREDIENTS: ALCOHOL 70 mL/100 1
INACTIVE INGREDIENTS: WATER 29 mL/100 1; ISOPROPYL ALCOHOL 1 mL/100 1; GLYCERIN 1 mL/100 1; PROPANEDIOL 0.5 mL/100 1; ALOE VERA LEAF 0.1 mL/100 1; .ALPHA.-TOCOPHEROL ACETATE 0.001 mL/100 1

Amazon Commerical Hand Sanitizer Wipes

Drug Facts

Active Ingredient

Ethyl alcohol 70%

Purpose

Antiseptic

Use

to decrease bacteria on the skin

Warnings

For external use only: hands

Flammable. Keep away from heat and flame.

When using this product

- keep out of eyes. In case of contact with eyes, flush thoroughly with water.
- avoid contact with broken skin
- do not inhale or ingest

Stop use and ask a doctor if

- irritation or redness develops
- condition persists for more than 72 hours

Keep out of reach of children. If swallowed, get medical help or contact a Poison Control Center right away.

Directions

Adults and children 2 years and over:

- wet hands thoroughly with the product and allow to dry without wiping
- not recommended for infants

Other Information

- do not store above 105°F
- may discolor some fabrics
- harmful to wood finishes and plastics

Inactive Ingredients

Aloe Barbadensis Leaf Juice, Glycerin, Isopropanol, Propanediol, Tocopheryl Acetate, Water

Distributed by:
Amazon.com Services, Inc.
410 Terry Avenue, N.
Seattle, WA 98109

PRINCIPAL DISPLAY PANEL - 160 Wipe Pouch Canister Label

amazon commercial

70% ETHYL
ALCOHOL

HAND SANITIZER
WIPES

160 WIPES

KILLS 99.99% OF GERMS INSTANTLY*
FAST AND EFFECTIVE
WITH ALOE AND VITAMIN E

FOR HAND SANITIZATION

NET CONTENTS: 160 WIPES 7 X 6 IN (17.8 X 15.2 CM)